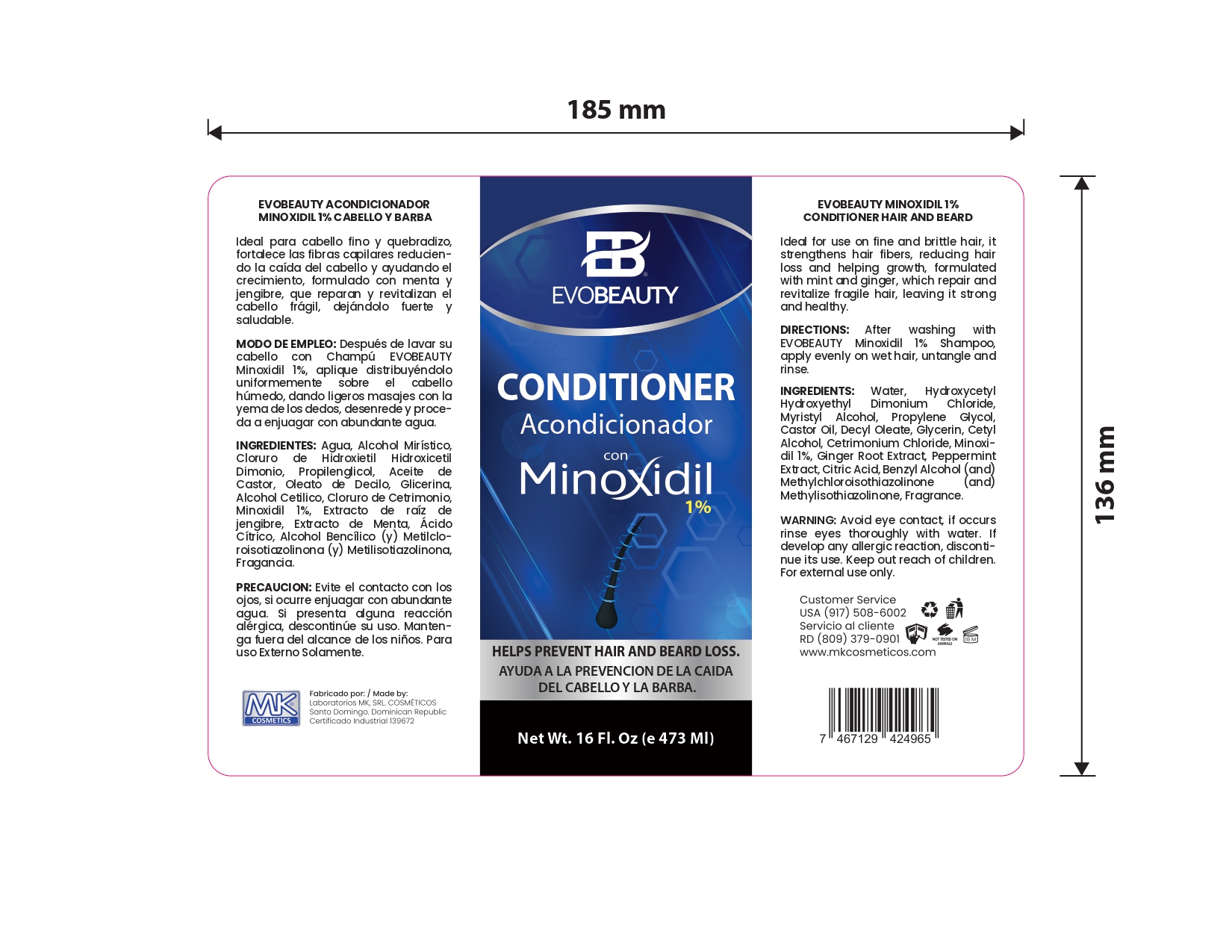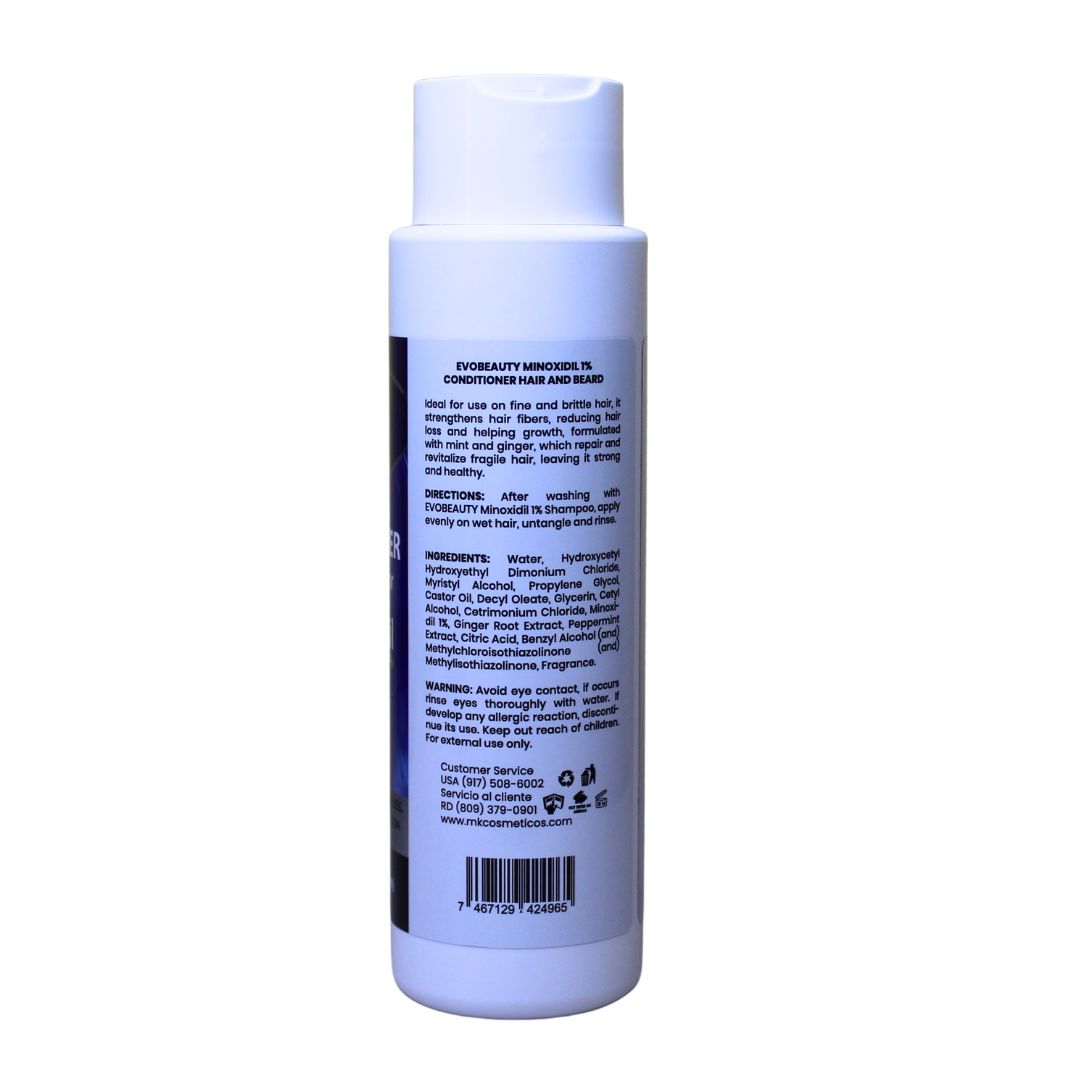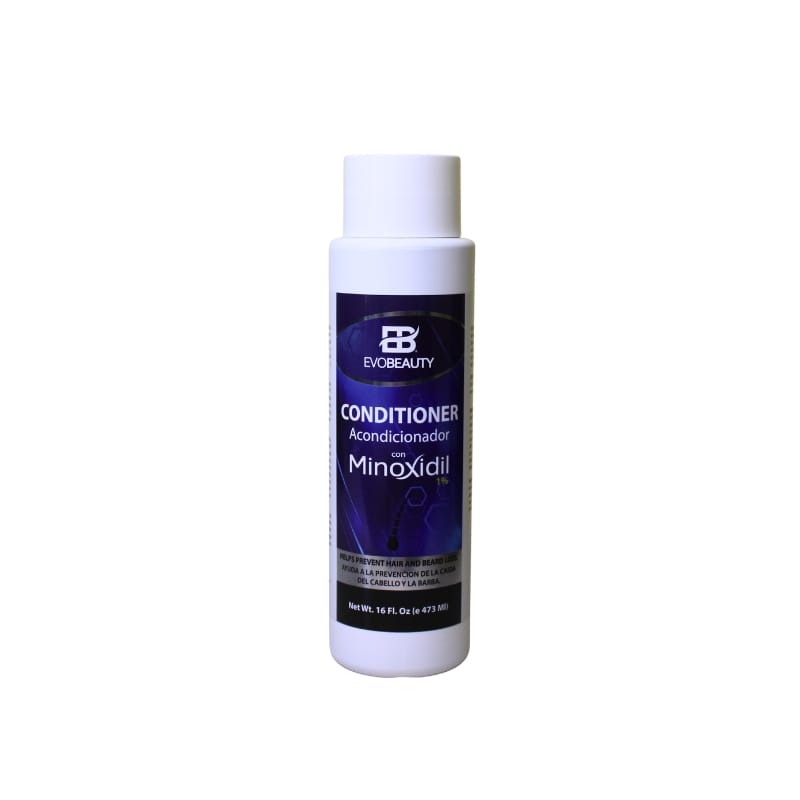 DRUG LABEL: hair acondicionador
NDC: 87022-008 | Form: RINSE
Manufacturer: LABORATORIO MK SRL
Category: otc | Type: HUMAN OTC DRUG LABEL
Date: 20250829

ACTIVE INGREDIENTS: MINOXIDIL 1 mg/473 mL
INACTIVE INGREDIENTS: CETYL ALCOHOL; CETRIMONIUM CHLORIDE; METHYLCHLOROISOTHIAZOLINONE; PEPPERMINT; DECYL OLEATE; HYDROXYCETYL HYDROXYETHYL DIMONIUM CHLORIDE; WATER; PROPYLENE GLYCOL 1,2-DISTEARATE; MYRISTYL ALCOHOL; METHYLISOTHIAZOLINONE; GINGER; CITRIC ACID; CASTOR OIL; GLYCERIN; .ALPHA.-(.ALPHA.-AMINOPROPYL)BENZYL ALCOHOL

INDICATIONS AND USAGE

After washing with EVOBEAUTY Minoxidil 1% Shampoo, apply evenly on wet hair, untangle and rinse.

INACTIVE INGREDIENT

Water, Hydroxycetyl Hydroxyethyl Dimonium Chloride, Myristyl Alcohol, Propylene Glycol, Castor Oil, Decyl Oleate, Glycerin, Cetyl Alcohol, Cetrimonium Chloride, Ginger Root Extract, Peppermint Extract, Citric Acid, Benzyl Alcohol (and) Methylchloroisothiazolinone (and) Methylisothiazolinone

WARNINGS

Avoid eye contact, if occurs rinse eyes thoroughly with water. If develop any allergic reaction, discontinue its use

INFORMATION FOR OWNERS/CAREGIVERS

Customer Service USA (917)508-6002

Customer Service RD (809)379-0900

www.mkcosmeticos.com

DOSAGE AND ADMINISTRATION

After washing with EVOBEAUTY Minoxidil 1% Shampoo, apply evenly on wet hair, untangle and rinse.

KEEP OUT OF REACH OF CHILDREN

Keep out reach of children. For external use only.

PURPOSE

growth and help prevent hair and beard loss. Revitalizes hair follicles and stimulates growth. it is mentioned at the front side of the box and also in the indications & usage section.

PACKAGE LABEL

This is the principal panel display side of the minoxidil hair conditioner 1%